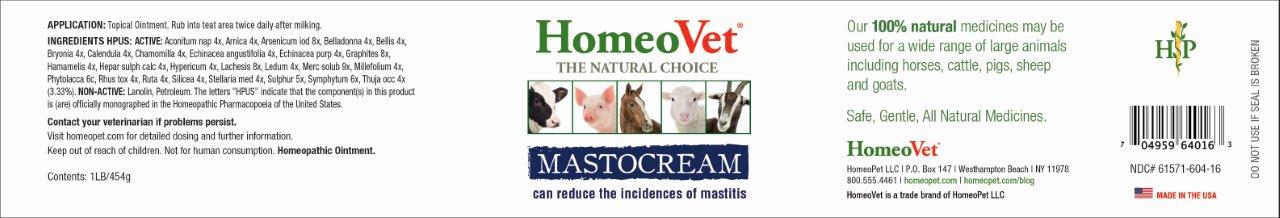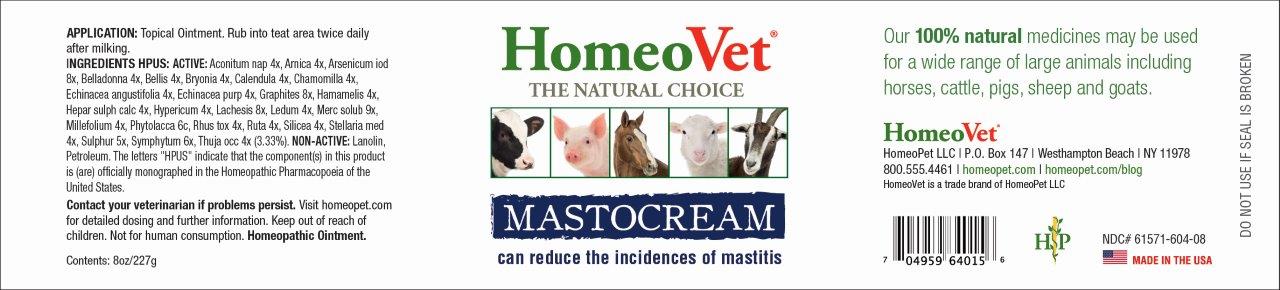 DRUG LABEL: Mastocream
NDC: 61571-604 | Form: SOLUTION
Manufacturer: HomeoPet LLC
Category: homeopathic | Type: OTC ANIMAL DRUG LABEL
Date: 20201203

ACTIVE INGREDIENTS: ACONITUM NAPELLUS 4 [hp_X]/227 g; ARNICA MONTANA 4 [hp_X]/227 g; ARSENIC TRIIODIDE 8 [hp_X]/227 g; ATROPA BELLADONNA 4 [hp_X]/227 g; BELLIS PERENNIS 4 [hp_X]/227 g; BRYONIA ALBA ROOT 4 [hp_X]/227 g; CALENDULA OFFICINALIS FLOWERING TOP 4 [hp_X]/227 g; MATRICARIA RECUTITA 4 [hp_X]/227 g; ECHINACEA ANGUSTIFOLIA 4 [hp_X]/227 g; ECHINACEA PURPUREA 4 [hp_X]/227 g; GRAPHITE 8 [hp_X]/227 g; HAMAMELIS VIRGINIANA ROOT BARK/STEM BARK 4 [hp_X]/227 g; CALCIUM SULFIDE 4 [hp_X]/227 g; HYPERICUM PERFORATUM 4 [hp_X]/227 g; LACHESIS MUTA VENOM 8 [hp_X]/227 g; LEDUM PALUSTRE TWIG 4 [hp_X]/227 g; MERCURIUS SOLUBILIS 9 [hp_X]/227 g; ACHILLEA MILLEFOLIUM 4 [hp_X]/227 g; PHYTOLACCA AMERICANA ROOT 6 [hp_C]/227 g; TOXICODENDRON PUBESCENS LEAF 4 [hp_X]/227 g; RUTA GRAVEOLENS FLOWERING TOP 4 [hp_X]/227 g; SILICON DIOXIDE 4 [hp_X]/227 g; STELLARIA MEDIA 4 [hp_X]/227 g; SULFUR 5 [hp_X]/227 g; COMFREY ROOT 6 [hp_X]/227 g; THUJA OCCIDENTALIS LEAFY TWIG 4 [hp_X]/227 g
INACTIVE INGREDIENTS: LANOLIN; PETROLATUM

Mastocream

Application

Topical Ointment. Rub into teat area twice daily after milking.

INGREDIENTS HPUS: ACTIVE:

Aconitum nap 4x, Arnica 4x, Arsenicum iod 8x, Belladonna 4x, Bellis 4x, Bryonia 4x, Calendula 4x, Chamomilla 4x, Echinacea angustifolia 4x, Echinacea purp 4x, Graphites 8x, Hamamelis 4x, Hepar sulph calc 4x, Hypericum 4x, Lachesis 8x, Ledum 4x, Merc solub 9x, Millefolium 4x, Phytolacca 6c, Rhus tox 4x, Ruta 4x, Silicea 4x, Stellaria med 4x, Sulphur 5x, Symphytum 6x, Thuja occ 4x.

INACTIVE INGREDIENT

Petroleum, Lanolin